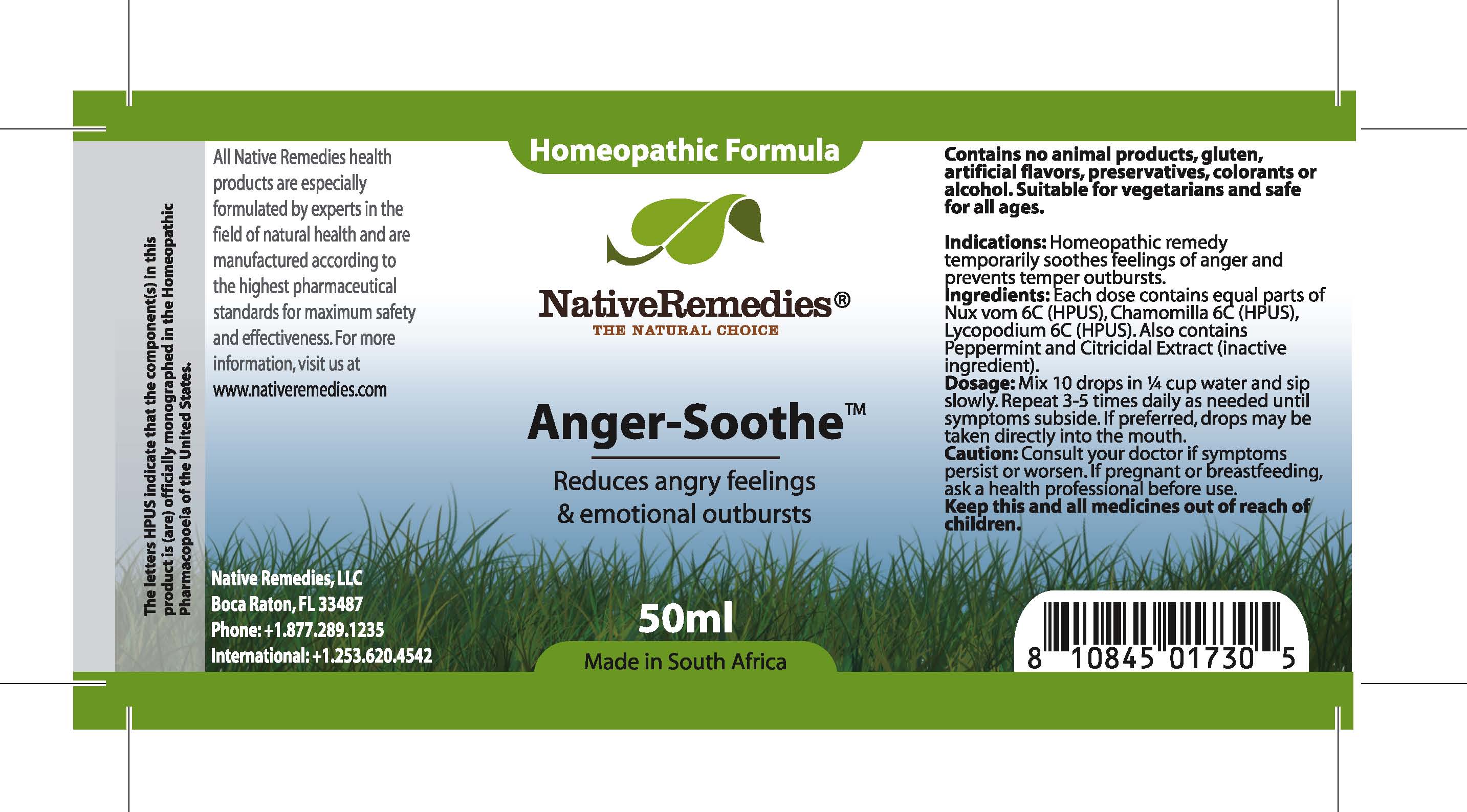 DRUG LABEL: AngerSoothe
NDC: 68647-178 | Form: TINCTURE
Manufacturer: Feelgood Health
Category: homeopathic | Type: HUMAN OTC DRUG LABEL
Date: 20100615

ACTIVE INGREDIENTS: STRYCHNOS NUX-VOMICA SEED 6 [hp_C]/50 mg; CHAMOMILE 5 [hp_C]/50 mg; LYCOPODIUM CLAVATUM SPORE 6 [hp_C]/50 mg; MINT 1 [hp_X]/10 mg
INACTIVE INGREDIENTS: GRAPEFRUIT SEED 1 1/0.25 mg; WATER 1 1/988.7 mg

ANGERSOOTHE

INDICATIONS AND USAGE

Indications: Homeopathic remedy soothes feelings of anger and prevents temper outbursts.

DOSAGE AND ADMINISTRATION

Dosage: Mix 10 drops in ¼ cup water and sip slowly. Repeat 3-5 times daily as needed until symptoms subside. If preferred, drops may be taken directly into the mouth

GENERAL PRECAUTIONS

Caution: Consult your doctor if symptoms persist or worsen. Keep this and all medicines out of reach of children.

DESCRIPTION

Reduces angry feelings and emotional outbursts.

ACTIVE INGREDIENT

Ingredients: Each dose contains equal parts of Nux vom (6C)(HPUS), Chamomilla (6C)(HPUS), Lycopodium (6C)(HPUS).

Peppermint and Citricidal Extract (inactive ingredient).

PREGNANCY

If pregnant or breastfeeding, ask a health professional before use.

USER SAFETY WARNINGS

Contains no animal products, gluten, artificial flavors, preservatives, colorants or alcohol. Suitable for vegetarians and safe for all ages.

PATIENT COUNSELING INFORMATION

All Native Remedies health products are especially formulated by experts in the field of natural health and are manufactured according to the highest pharmaceutical standards for maximum safety and effectiveness. For more information, visit us at www.nativeremedies.com

Distributed by

Native Remedies, LLC

6531 Park of Commerce Blvd.

Suite 160

Boca Raton, FL 33487

Phone: +1.877.289.1235

International: +1.561.999.8857

The letters HPUS indicate that the component(s) in this product is (are) officially monographed in the Homeopathic Pharmacopoeia of the United States.